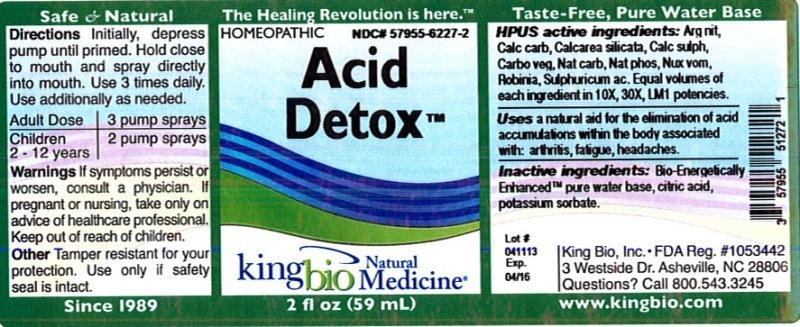 DRUG LABEL: Acid Detox
NDC: 57955-6227 | Form: LIQUID
Manufacturer: King Bio Inc.
Category: homeopathic | Type: HUMAN OTC DRUG LABEL
Date: 20120402

ACTIVE INGREDIENTS: SILVER NITRATE 10 [hp_X]/59 mL; OYSTER SHELL CALCIUM CARBONATE, CRUDE 10 [hp_X]/59 mL; CALCIUM SILICATE 10 [hp_X]/59 mL; CALCIUM SULFATE ANHYDROUS 10 [hp_X]/59 mL; ACTIVATED CHARCOAL 10 [hp_X]/59 mL; SODIUM CARBONATE 10 [hp_X]/59 mL; SODIUM PHOSPHATE, DIBASIC, HEPTAHYDRATE 10 [hp_X]/59 mL; STRYCHNOS NUX-VOMICA SEED 10 [hp_X]/59 mL; ROBINIA PSEUDOACACIA BARK 10 [hp_X]/59 mL; SULFURIC ACID 10 [hp_X]/59 mL
INACTIVE INGREDIENTS: WATER; CITRIC ACID MONOHYDRATE; POTASSIUM SORBATE

Acid Detox

Active Ingredients

Official HPUS:

Argentum nitricum, Calcarea carbonica, Calcarea silicata, Calcarea sulphurica, Carbo vegetabilis, Natrum carbonicum, Natrum phosphoricum, Nux vomica, Robinia pseudoacacia, Sulphuricum acidum. Equal volumes of each ingredient in 10X, 30X, LM1 potencies.

Inactive Ingredient

Equal volumes of each ingredient in a Bio-Energetically Enhanced™ pure water base, citric acid, potassium sorbate.

Dosage and Administration

Directions Initially, depress pump until primed. Hold close to mouth and spray one dose directly into mouth. Use 3 times per day. Use additionally as needed.

Adult Dose 3 pump sprays

Children 2-12 years 2 pump sprays

Purpose

Uses a natural aid for the elimination of acid accumulations within the body associated with arthritis, fatigue, and headaches.

INDICATIONS AND USAGE

Uses a natural aid for the elimination of acid accumulations within the body associated with:

- arthritis
- fatigue
- headaches

Warnings

Warnings if symptoms persist or worsen, or if pregnant or nursing, take only on advice of a healthcare professional. Keep out of reach of children.

Tamper resistant for your protection. Use only if safety seal in intact.

Keep out of reach of children.